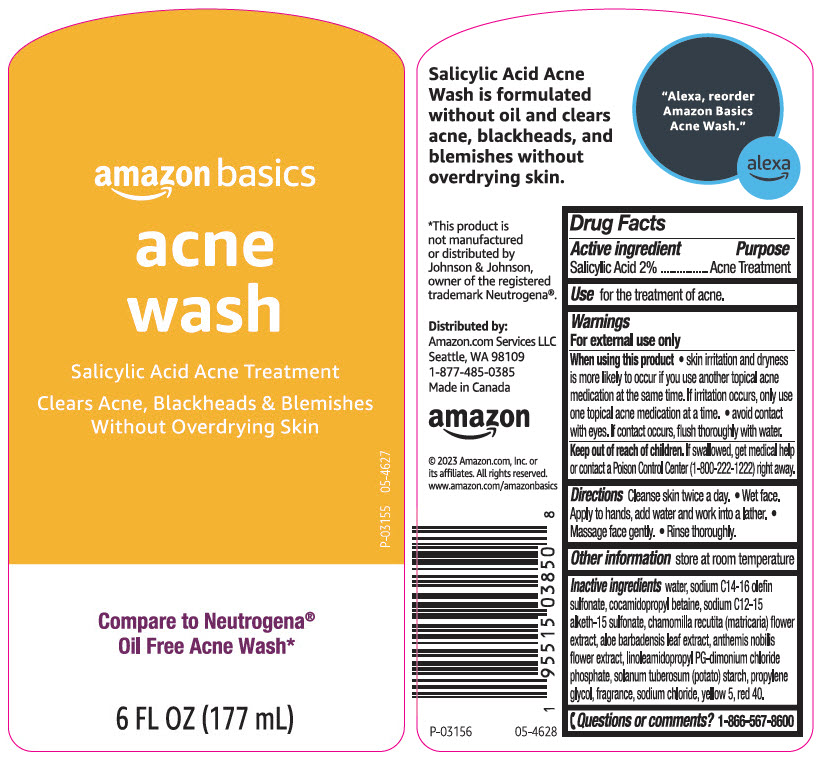 DRUG LABEL: Amazon Basics Acne Wash
NDC: 72288-955 | Form: LIQUID
Manufacturer: AMAZON.COM SERVICES LLC
Category: otc | Type: HUMAN OTC DRUG LABEL
Date: 20241115

ACTIVE INGREDIENTS: Salicylic Acid 20 mg/1 mL
INACTIVE INGREDIENTS: Water; Sodium C14-16 Olefin Sulfonate; Cocamidopropyl Betaine; SODIUM C12-15 ALKETH-15 SULFONATE; CHAMOMILE; ALOE VERA LEAF; CHAMAEMELUM NOBILE FLOWER; LINOLEAMIDOPROPYL PROPYLENE GLYCOL-DIMONIUM CHLORIDE PHOSPHATE; STARCH, POTATO; Propylene Glycol; Sodium Chloride; FD&C YELLOW NO. 5; FD&C RED NO. 40

Amazon Basics Acne Wash
Acne treatment

Drug Facts

Active ingredient

Salicylic Acid 2%

Purpose

Acne treatment

Use

for the treatment of acne.

Warnings

For external use only

When using this product

- skin irritation and dryness is more likely to occur if you use another topical acne medication at the same time. If irritation occurs, only use one topical medication at a time
- avoid contact with eyes. If contact occurs, flush thoroughly with water.

Keep out of reach of children. If swallowed, get medical help or contact a Poison Control Center (1-800-222-1222) right away.

Directions

Cleanse skin twice a day

- Wet face. Apply to hands, add water and work into a lather.
- Massage face gently.
- Rinse thoroughly.

Other information

store at room temperature

Inactive ingredients

Water, Sodium C14-16 Olefin Sulfonate, Cocamidopropyl Betaine, Sodium C12-15 Alketh-15 Sulfonate, Chamomilla Recutita (Matricaria) Flower Extract, Aloe Barbadensis Leaf Extract, Anthemis Nobilis Flower Extract, Linoleamidopropyl PG-Dimonium Chloride Phosphate, Solanum Tuberosum (Potato) Starch, Propylene Glycol, Fragrance, Sodium Chloride, Yellow 5, Red 40.

Questions or comments?

1-866-567-8600

Distributed by:
Amazon.com Services LLC
Seattle, WA 98109

PRINCIPAL DISPLAY PANEL - 177 mL Bottle Label

amazon basics

acne
wash

Salicylic Acid Acne Treatment

Clears Acne, Blackheads & Blemishes
Without Overdrying Skin

P-03155 05-4627

Compare to Neutrogena®
Oil Free Acne Wash*

6 FL OZ (177 mL)